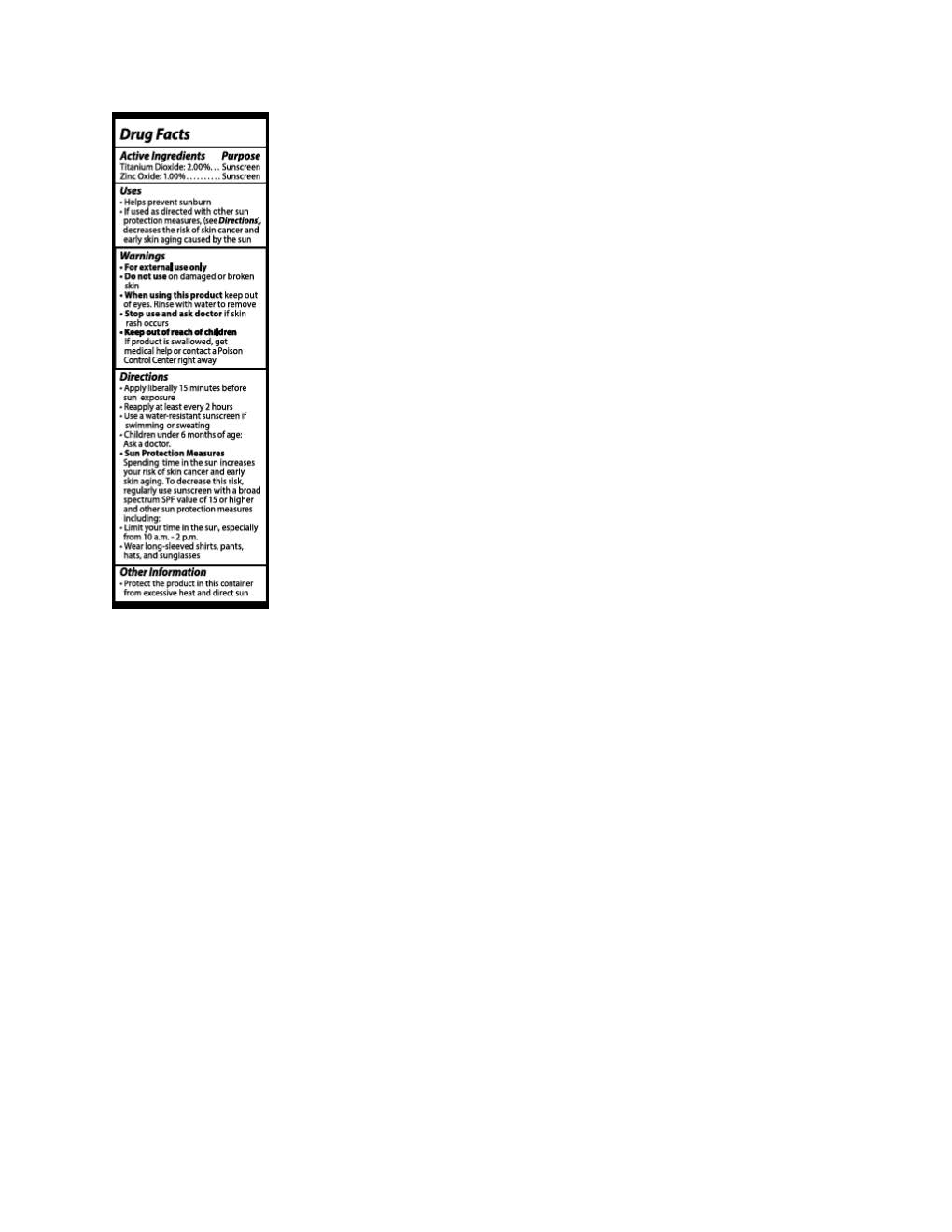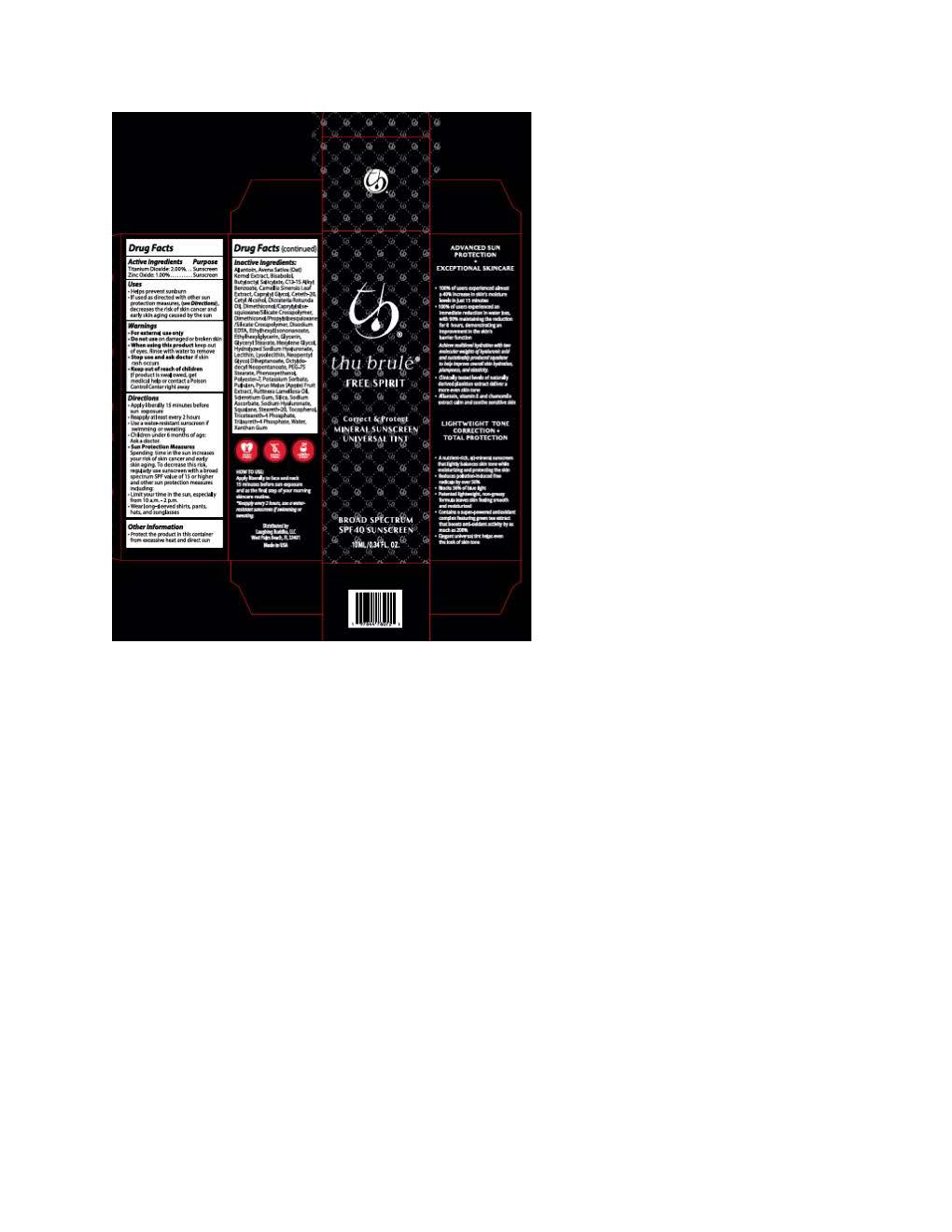 DRUG LABEL: Thu Brule Free Spirit Correct and Protect
NDC: 83859-0400 | Form: LOTION
Manufacturer: Laughing Buddha LLC
Category: otc | Type: HUMAN OTC DRUG LABEL
Date: 20251114

ACTIVE INGREDIENTS: ZINC OXIDE 9.7 mg/1 mL; TITANIUM DIOXIDE 19.4 mg/1 mL
INACTIVE INGREDIENTS: GLYCERIN; CETETH-20; RUTTNERA LAMELLOSA OIL; POTASSIUM SORBATE; POLYESTER-7; LECITHIN, SOYBEAN; SODIUM ASCORBATE; TOCOPHEROL; PULLULAN; CAPRYLYL GLYCOL; XANTHAN GUM; NEOPENTYL GLYCOL DIHEPTANOATE; PHENOXYETHANOL; .ALPHA.-BISABOLOL, (+)-; ALLANTOIN; TRICETEARETH-4 PHOSPHATE; STEARETH-20; HEXYLENE GLYCOL; SILICON DIOXIDE; SODIUM CITRATE; DIMETHICONOL/PROPYLSILSESQUIOXANE/SILICATE CROSSPOLYMER (450000000 MW); ETHYLHEXYL ISONONANOATE; FERRIC OXIDE YELLOW; DICRATERIA ROTUNDA OIL; FERRIC OXIDE RED; OCTYLDODECYL NEOPENTANOATE; SQUALANE; ETHYLHEXYLGLYCERIN; PEG-75 STEARATE; ALKYL (C12-15) BENZOATE; TRILAURETH-4 PHOSPHATE; BUTYLOCTYL SALICYLATE; WATER; CETYL ALCOHOL

Thu Brule Free Spirit Correct and Protect